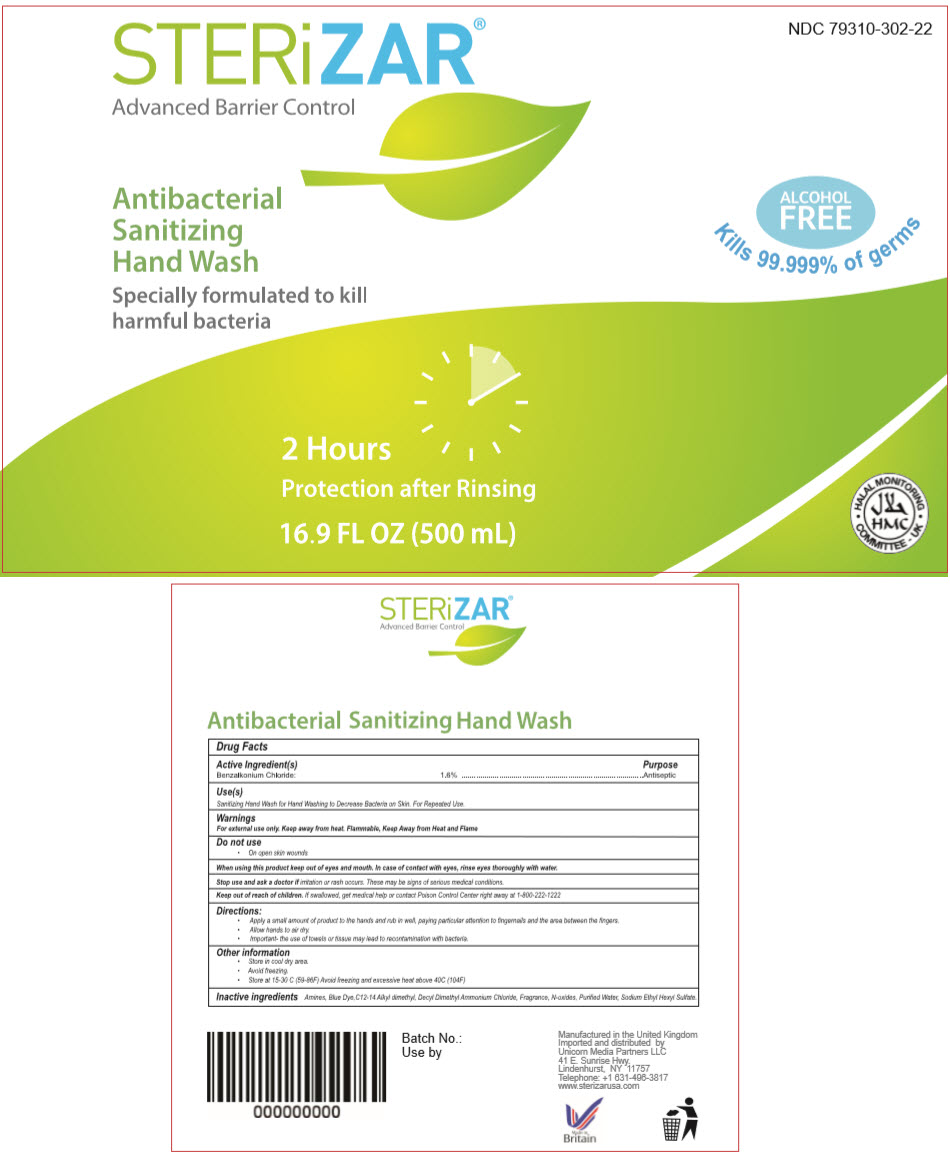 DRUG LABEL: STERiZAR 
NDC: 79310-302 | Form: SOAP
Manufacturer: Unicorn Media Partners LLC
Category: otc | Type: HUMAN OTC DRUG LABEL
Date: 20210114

ACTIVE INGREDIENTS: Benzalkonium Chloride 16 mg/1 mL
INACTIVE INGREDIENTS: DIDECYLDIMONIUM CHLORIDE; SODIUM ETHASULFATE; WATER; HYDROXYETHYL CELLULOSE, UNSPECIFIED

STERiZAR®
Advanced Barrier Control

Drug Facts

Active Ingredient(s)

Benzalkonium Chloride 1.6 %

Purpose

Antiseptic

Use

Sanitizing Hand Wash for Hand Washing to Decrease Bacteria on Skin. For Repeated Use.

Warnings

For external use only. Keep away from heat. Flammable, Keep Away from Heat and Flame

Do not use

- On open skin wounds

When using this product keep out of eyes and mouth. In case of contact with eyes, rinse eyes thoroughly with water.

Stop use and ask a doctor if irritation or rush occurs These may be sign of serious medical conditions.

Keep out of reach of children. If swallowed, get medical help or contact Poison Control Center right away at 1-800-222-1222

Directions

- Apply a small amount of product to the hands and rub in well, paying particular attention to fingernails and the area between the fingers.
- Allow hands to air dry.
- Important- the use of towels or tissue may lead to recontamination with bacteria.

Other information

- Store in cool dry area.
- Avoid freezing
- Store at 15-30 C (59-86F) Avoid freezing and excessive heat above 40C (104F)

Inactive ingredients

Amines, Blue Dye,C12-14 Alkyl dimethyl, Decyl Dimethyl Ammonium Chloride, Fragrance, N-oxides, Purified Water, Sodium Ethyl Hexyl Sulfate.

Imported and distributed by
Unicorn Media Partners LLC
41 E. Sunrise Hwy.
Lindenhurst, NY 11757

PRINCIPAL DISPLAY PANEL - 500 mL Bottle Label

NDC 79310-302-22

STERiZAR®
Advanced Barrier Control

Antibacterial
Sanitizing
Hand Wash

Specially formulated to kill
harmful bacteria

ALCOHOL
FREE
Kills 99.999% of germs

2 Hours
Protection after Rinsing

16.9 FL OZ (500 mL)

• HALAL MONITORING •
COMMITTEE - UK